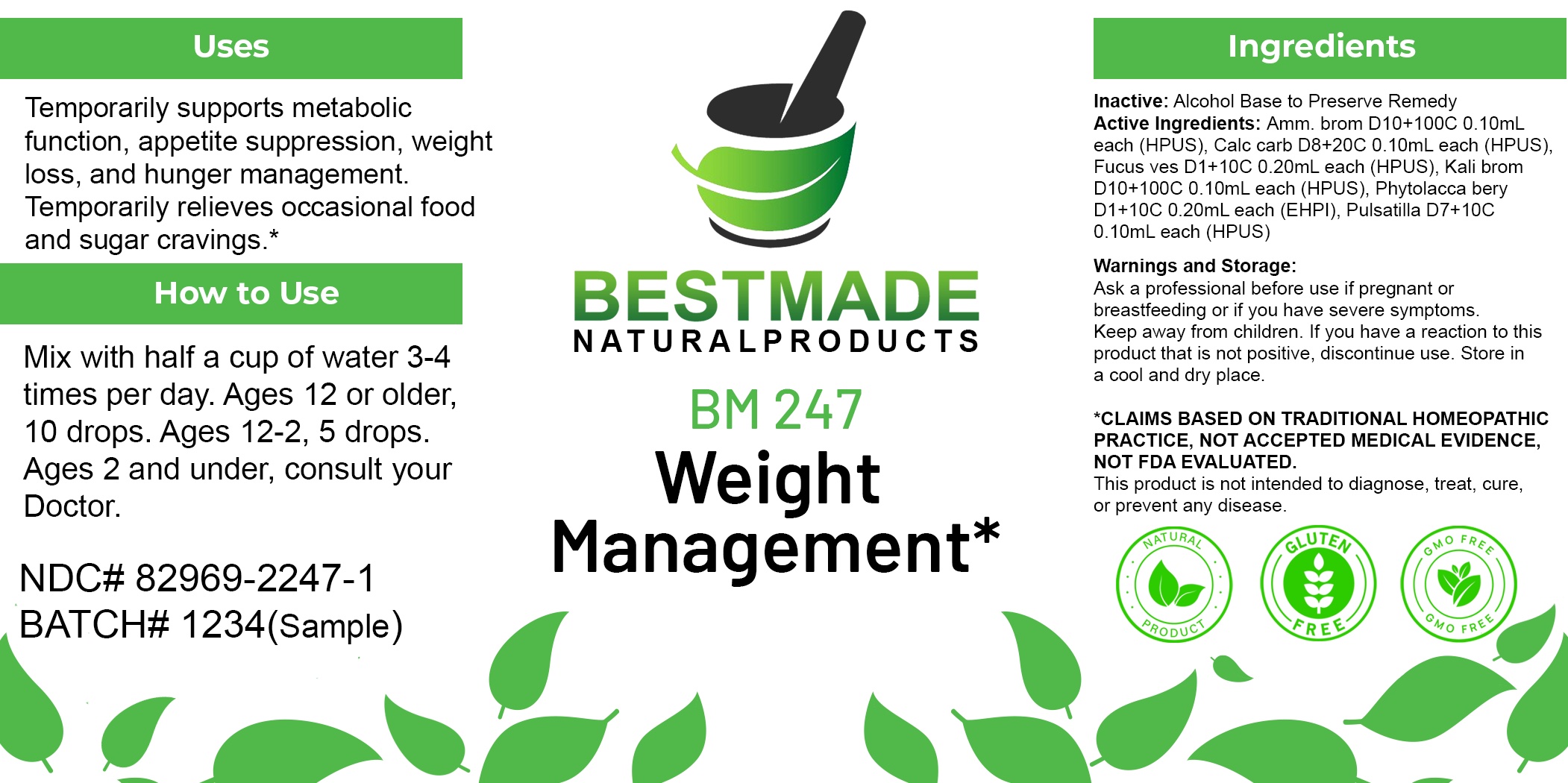 DRUG LABEL: Bestmade Natural Products BM247
NDC: 82969-2247 | Form: LIQUID
Manufacturer: Bestmade Natural Products
Category: homeopathic | Type: HUMAN OTC DRUG LABEL
Date: 20250305

ACTIVE INGREDIENTS: PHYTOLACCA AMERICANA FRUIT 30 [hp_C]/30 [hp_C]; OYSTER SHELL CALCIUM CARBONATE, CRUDE 30 [hp_C]/30 [hp_C]; AMMONIUM BROMIDE 30 [hp_C]/30 [hp_C]; PULSATILLA VULGARIS 30 [hp_C]/30 [hp_C]; FUCUS VESICULOSUS 30 [hp_C]/30 [hp_C]; POTASSIUM BROMIDE 30 [hp_C]/30 [hp_C]
INACTIVE INGREDIENTS: ALCOHOL 30 [hp_C]/30 [hp_C]

BM247

DOSAGE AND ADMINISTRATION

How to Use

Mix with half a cup of water 3-4 times per day. Ages 12 or older, 10 drops. Ages 12-2, 5 drops. Ages 2 and under, consult your Doctor.

Inactive:

Alcohol Base to Preserve Product

ACTIVE INGREDIENT

Active Ingredients: Amm. brom D10+100C 0.10mL each (HPUS), Calc carb D8+20C 0.10mL each (HPUS), Fucus ves D1+10C 0.20mL each (HPUS), Kali brom D10+100C 0.10mL each (HPUS), Phytolacca bery D1+10C 0.20mL each (EHPI), Pulsatilla D7+10C 0.10mL each (HPUS)

KEEP OUT OF REACH OF CHILDREN

Warnings and Storage:

Ask a professional before use if pregnant or breastfeeding or if you have severe symptoms.

Keep away from children. If you have a reaction to this product that is not positive, discontinue use. Store in a cool and dry place

*CLAIMS BASED ON TRADITIONAL HOMEOPATHIC PRACTICE, NOT ACCEPTED MEDICAL EVIDENCE NOT FDA EVALUATED.
This product is not intended to diagnose, treat, cure, or prevent any disease.

Warnings and Storage:

Ask a professional before use if pregnant or breastfeeding or if you have severe symptoms.

Keep away from children. If you have a reaction to this product that is not positive, discontinue use. Store in a cool and dry place

*CLAIMS BASED ON TRADITIONAL HOMEOPATHIC PRACTICE, NOT ACCEPTED MEDICAL EVIDENCE NOT FDA EVALUATED.
This product is not intended to diagnose, treat, cure, or prevent any disease.

Uses
Temporarily supports metabolic function, appetite suppression, weight loss, and hunger management. Temporarily relieves occasional food and sugar cravings.*

Uses
Temporarily supports metabolic function, appetite suppression, weight loss, and hunger management. Temporarily relieves occasional food and sugar cravings.*

Entire package label